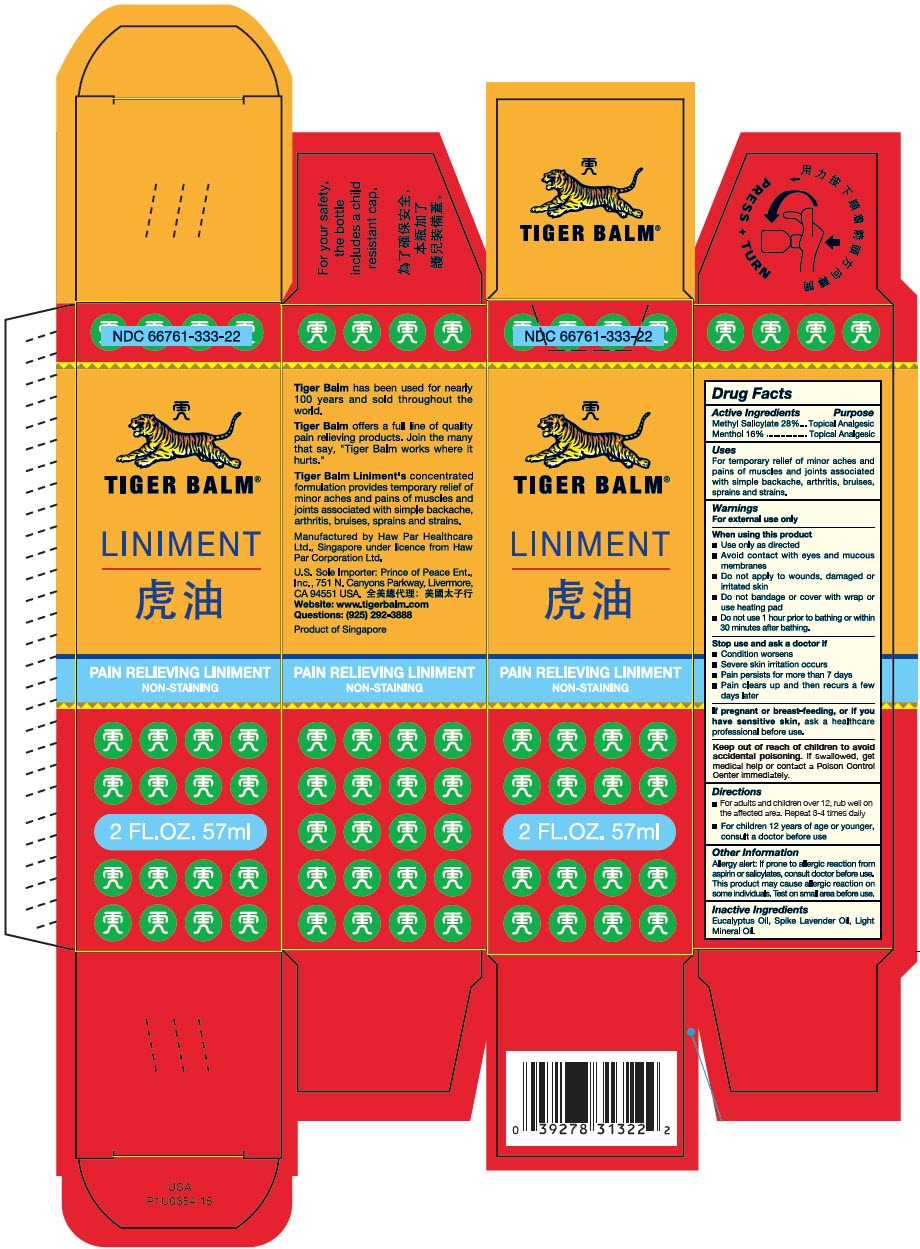 DRUG LABEL: Tiger Balm
NDC: 66761-333 | Form: LINIMENT
Manufacturer: Haw Par Healthcare Ltd.
Category: otc | Type: HUMAN OTC DRUG LABEL
Date: 20241114

ACTIVE INGREDIENTS: Methyl Salicylate 260.4 mg/1 mL; Menthol, Unspecified Form 148.8 mg/1 mL
INACTIVE INGREDIENTS: Eucalyptus oil; spike lavender oil; light mineral oil

TIGER BALM®
LINIMENT

Drug Facts

ACTIVE INGREDIENT

Active Ingredients | Purpose
Methyl Salicylate 28% | Topical Analgesic
Menthol 16% | Topical Analgesic

Uses

For temporary relief of minor aches and pains of muscles and joints associated with simple backache, arthritis, bruises, sprains and strains.

Warnings

For external use only

When using this product

- Use only as directed
- Avoid contact with eyes and mucous membranes
- Do not apply to wounds, damaged or irritated skin
- Do not bandage or cover with wrap or use heating pad
- Do not use 1 hour prior to bathing or within 30 minutes after bathing.

Stop use and ask a doctor if

- Condition worsens
- Severe skin irritation occurs
- Pain persists for more than 7 days
- Pain clears up and then recurs a few days later

PREGNANCY OR BREAST FEEDING

If pregnant or breast-feeding, or if you have sensitive skin, ask a healthcare professional before use.

Keep out of reach of children. If swallowed, get medical help or contact a Poison Control Center immediately.

Directions

- For adults and children over 12, rub well on the affected area. Repeat 3-4 times daily
- For children 12 years of age or younger, consult a doctor before use

Other Information

Allergy alert

If prone to allergic reaction from aspirin or salicylates, consult doctor before use. This product may cause allergic reaction on some individuals. Test on small area before use.

Inactive Ingredients

Eucalyptus Oil, Spike Lavender Oil, Light Mineral Oil.

Questions

(925) 292-3888

Manufactured by Haw Par Healthcare
Ltd., Singapore under licence from Haw
Par Corporation Ltd.

PRINCIPAL DISPLAY PANEL - 57 ml Bottle Box

NDC 66761-333-22

TIGER BALM®

LINIMENT

PAIN RELIEVING LINIMENT
NON-STAINING

2 FL.OZ. 57ml